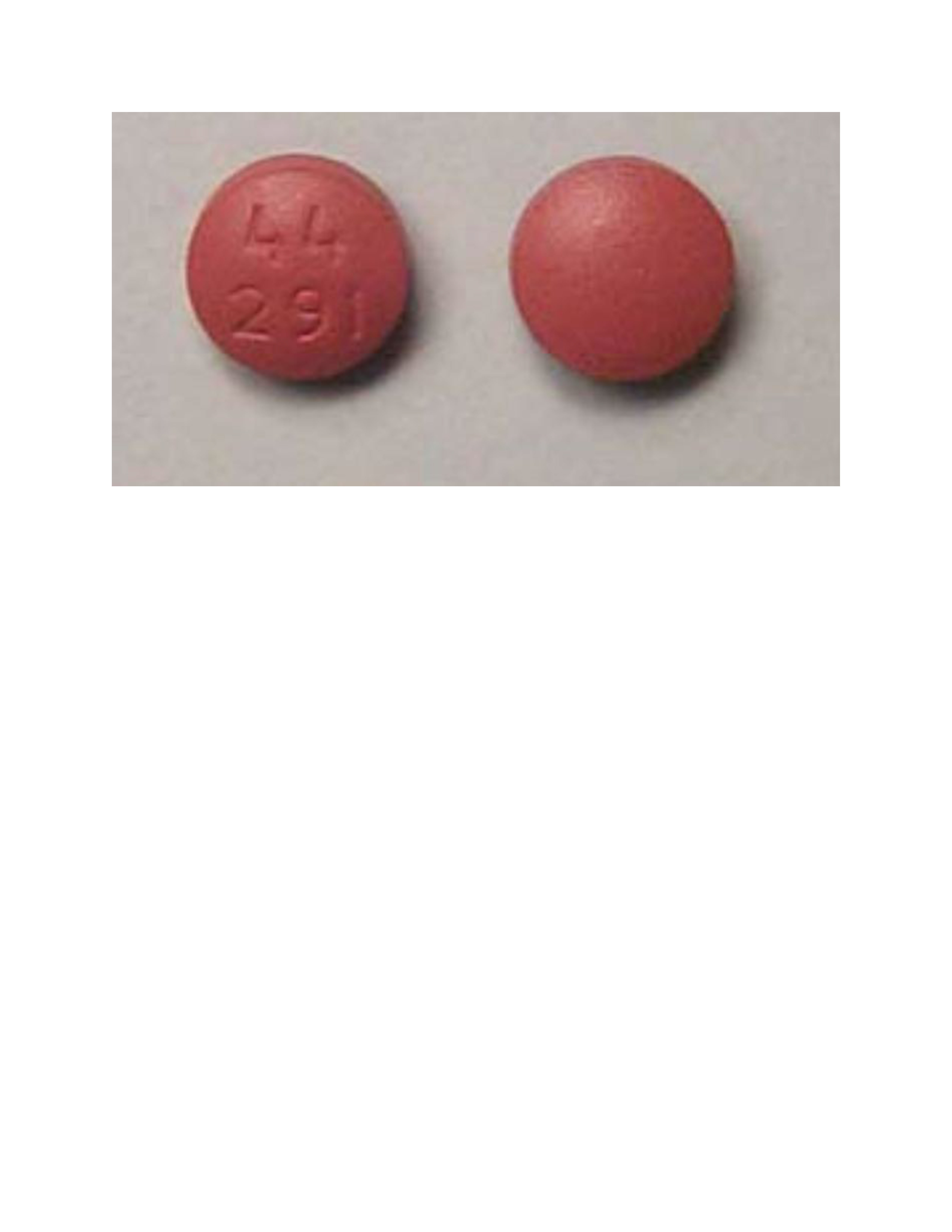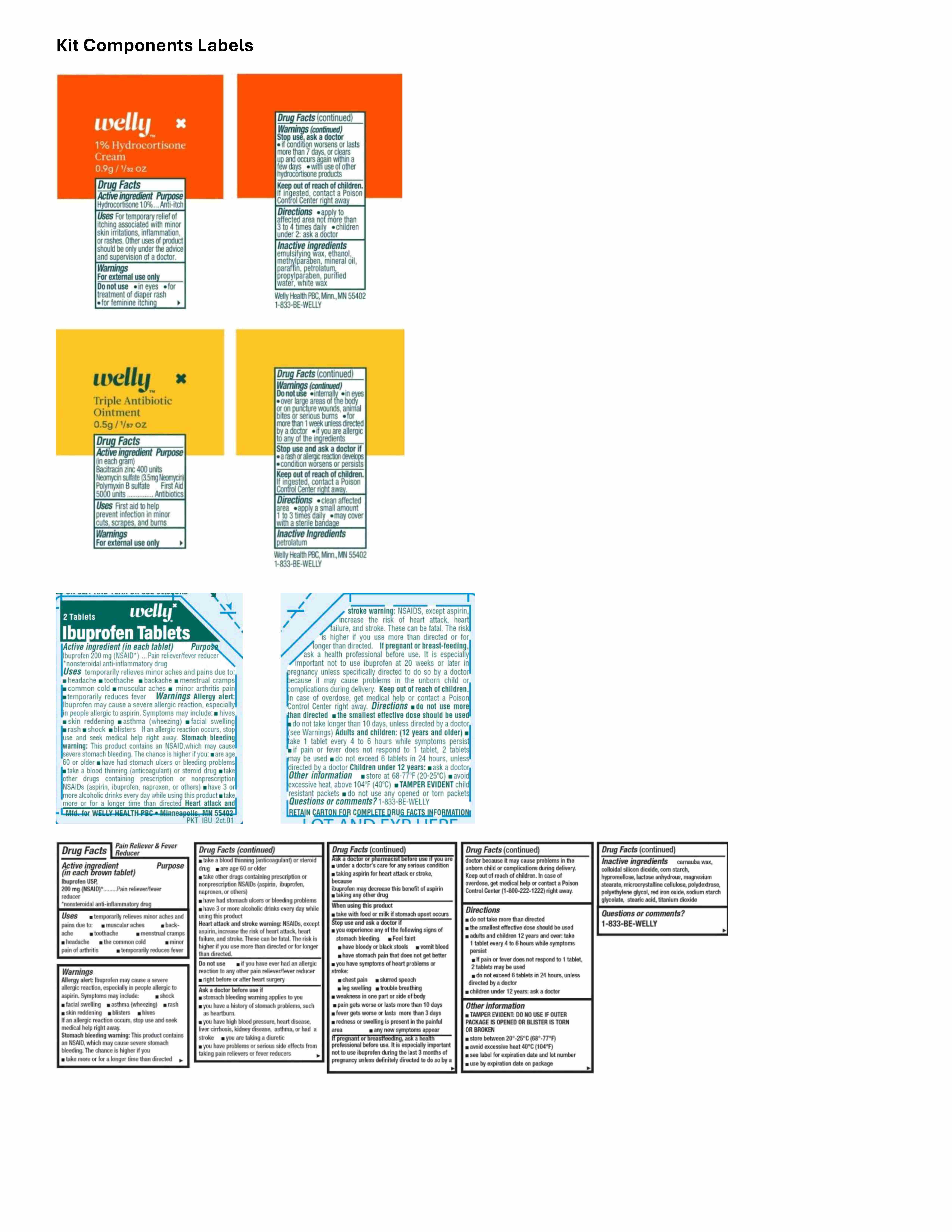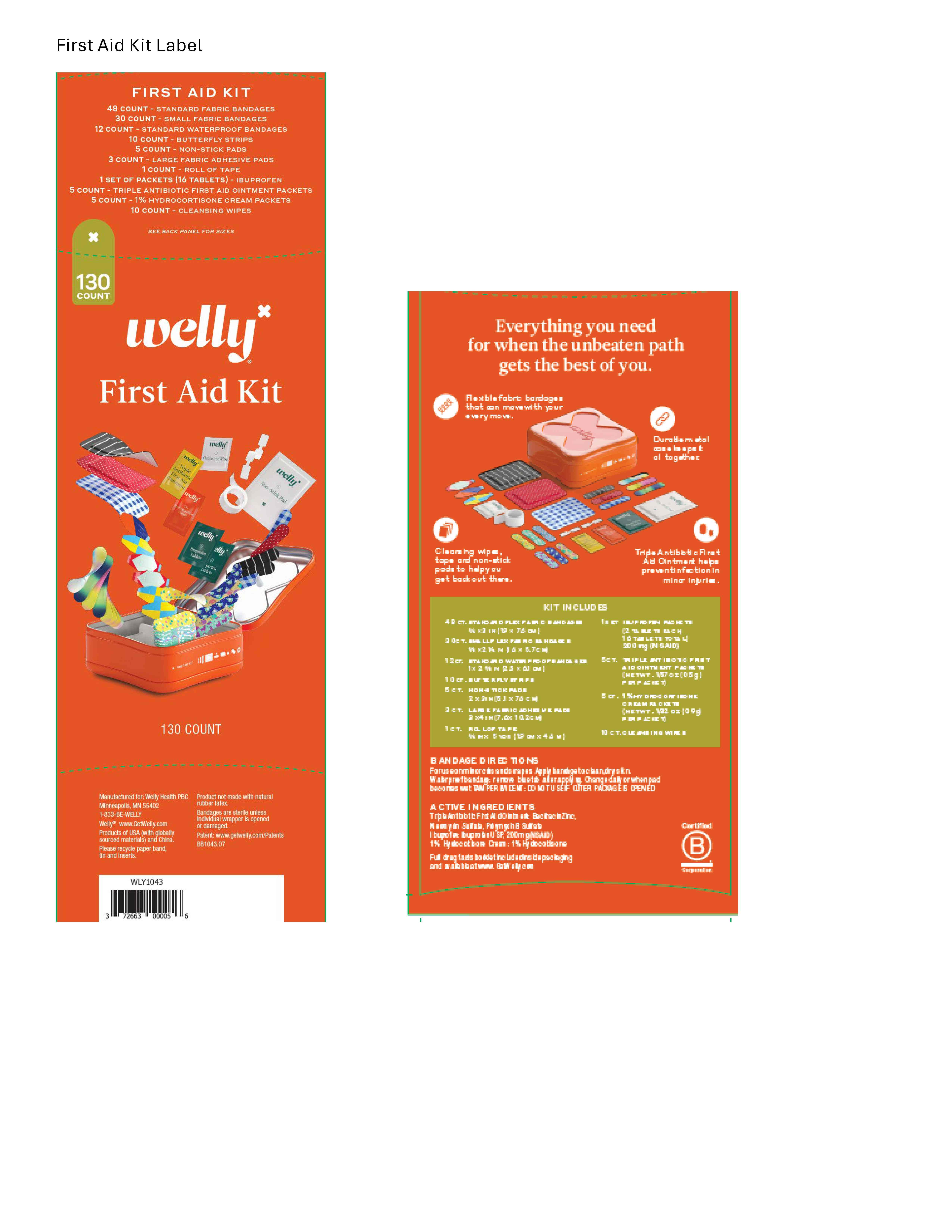 DRUG LABEL: Welly First Aid Kit
NDC: 72663-152 | Form: KIT | Route: TOPICAL
Manufacturer: Welly Health PBC
Category: otc | Type: HUMAN OTC DRUG LABEL
Date: 20250511

ACTIVE INGREDIENTS: HYDROCORTISONE 1 g/1 mL; BACITRACIN ZINC 6 mg/1 mL; NEOMYCIN SULFATE 3.5 mg/1 mL; POLYMYXIN B SULFATE 0.77 mg/1 mL; IBUPROFEN 200 mg/1 1
INACTIVE INGREDIENTS: ALCOHOL; METHYLPARABEN; MINERAL OIL; PARAFFIN; PETROLATUM; PROPYLPARABEN; WATER; WHITE WAX; PETROLATUM; CARNAUBA WAX; SILICON DIOXIDE; STARCH, CORN; HYPROMELLOSE, UNSPECIFIED; ANHYDROUS LACTOSE; MAGNESIUM STEARATE; MICROCRYSTALLINE CELLULOSE; POLYDEXTROSE; POLYETHYLENE GLYCOL, UNSPECIFIED; FERRIC OXIDE RED; STEARIC ACID; TITANIUM DIOXIDE

Welly First Aid Kit

1% Hydrocortisone Cream

Drug Facts

Active ingredient

Hydrocortisone 1.0%

Purpose

Anti-itch

Uses

- For temporary relief of itching associated with minor skin irritations, inflammation, or rashes.
- Other uses of product should be only under the advice and supervision of a doctor.

Warnings

For external use only

Do not use

- in eyes
- for treatment of diaper rash
- for feminine itching

Stop use, ask a doctor

- if condition worsens or lasts more than 7 days, or clears up and occurs again within a few days
- with use of other hydrocortisone products

Keep out of reach of children. If ingested, contact a Poison Control Center right away

Directions

- apply to affected area not more than 3 to 4 times daily
- children under 2: ask a doctor

Inactive ingredients

emulsifying wax, ethanol, methylparaben, mineral oil, paraffin, petrolatum, propylparaben, purified water, white wax

Triple Antibiotic Ointment

Drug Facts

Active Ingredient (in each gram)

Bacitracin zinc 400 units

Neomycin sulfate (3.5mg Neomycin)

Polymyxin B sulfate 5000 units

Purpose

First Aid Antibiotics

Uses

First aid to help prevent infection in minor cuts, scrapes and burns

Warnings

For external use only

Do not use

- internally
- in eyes
- over large areas of the body or on puncture wounds, animal bites or serious burns
- for more than 1 week unless directed by a doctor
- if you are allergic to any of the ingredients

Stop use and ask a doctor if

- a rash or allergic reactions develops
- condition worsens or persists

Keep out of reach of children. If ingested, contact a Poison Control Center right away.

Directions

- clean affected area
- apply a small amount 1 to 3 times daily
- may cover with a sterile bandage

Inactive Ingredients

petrolatum

Pain Relief and Fever Reducer

Drug Facts

Active ingredient (in each brown tablet)

Ibuprofen USP, 200 mg (NSAID)*

*nonsteroidal anti-inflammatory drug

Purpose

Pain reliever/fever reducer

Uses

- temporarily relieves minor aches and pains due to:
- muscular aches
- backache
- toothache
- menstrual cramps
- headache
- the common cold
- minor pain of arthritis
- temporarily reduces fever

Warnings

Allergy alert: Ibuprofen may cause a severe allergic reaction, especially in people allergic to aspirin. Symptoms may include:

- shock
- facial swelling
- asthma (wheezing)
- rash
- skin reddening
- blisters
- hives

If an allergic reaction occurs, stop use and seek medical help right away.

Stomach bleeding warning: This product contains an NSAID, which may cause severe stomach bleeding. The chance is higher if you

- take more or for a longer time than directed
- take a blood thinning (anticoagulant) or steroid drug
- take other drugs containing prescription or nonprescription NSAIDs (aspirin, ibuprofen, naproxen, or others)
- have had stomach ulcers or bleeding problems
- have 3 or more alcoholic drinks every day while using this product

Heart attack and stroke warning: NSAIDs, except aspirin, increase the risk of heart attack, heart failure, and stroke. These can be fatal. The risk is higher if you use more than directed or for longer than directed.

Do not use

- if you have ever had an allergic reaction to any other pain reliever/fever reducer
- right before or after heart surgery

Ask a doctor before use if

- stomach bleeding warning applies to you
- you have a history of stomach problems, such as heartburn.
- you have high blood pressure, heart disease, liver cirrhosis, kidney disease, asthma, or had a stroke
- you are taking a diuretic
- you have problems or serious side effects from taking pain relievers or fever reducers

Ask a doctor or pharmacist before use if you are

- under a doctor’s care for any serious condition
- taking aspirin for heart attack or stroke, because ibuprofen may decrease this benefit of aspirin
- taking any other drug

When using this product

- take with food or milk if stomach upset occurs

Stop use and ask a doctor if

- you experience any of the following signs of stomach bleeding.
- Feel faint
- have bloody or black stools
- vomit blood
- have stomach pain that does not get better
- you have symptoms of heart problems or stroke:
- chest pain
- slurred speech
- leg swelling
- trouble breathing
- weakness in one part or side of body
- pain gets worse or lasts more than 10 days
- fever gets worse or lasts more than 3 days
- redness or swelling is present in the painful area
- any new symptoms appear

If pregnant or breastfeeding,
ask a health professional before use. It is especially important not to use ibuprofen during the last 3 months of pregnancy unless definitely directed to do so by a doctor because it may cause problems in the unborn child or complications during delivery.

Keep out of reach of children. In case of overdose, get medical help or contact a Poison Control Center (1-800-222-1222) right away.

Directions

- do not take more than directed
- the smallest effective dose should be used
- adults and children 12 years and over: take 1 tablet every 4 to 6 hours while symptoms persist
- If pain or fever does not respond to 1 tablet, 2 tablets may be used
- do not exceed 6 tablets in 24 hours, unless directed by a doctor
- children under 12 years: ask a doctor

Other information

- TAMPER EVIDENT: DO NO USE IF OUTER PACKAGE IS OPENED OR BLISTER IS TORN OR BROKEN
- store between 20°-25°C (68°-77°F)
- avoid excessive heat 40°C (104°F)
- see label for expiration date and lot number
- use by expiration date on package

Inactive ingredients

carnauba wax, colloidal silicon dioxide, corn starch, hypromellose, lactose anhydrous, magnesium stearate, microcrystalline cellulose, polydextrose, polyethylene glycol, red iron oxide, sodium starch glycolate, stearic acid, titanium dioxide

Questions or comments?

1-833-BE-WELLY

First Aid Kit

LARGE FIRST AID KIT TO COVER ANY BUMP, BRUISE OR SCRAPE.

Everything you need for when the unbeaten path gets the best of you.

Flexible fabric bandages that can move with your every move.

Durable metal case keeps it all together.

Cleansing wipes, tape and non-stick pads to help you get back out there.

Triple Antibiotic ointment helps prevent infection.

KIT INCLUDES

48 COUNT - STANDARD FABRIC BANDAGES

30 COUNT - SMALL FABRIC BANDAGES

3 COUNT - THICK STRIP FLEX FABRIC BANDAGES (2"x4")

12 COUNT - WATERPROOF BANDAGES

1 COUNT - ROLL OF TAPE

5 COUNT - NON STICK PADS

10 COUNT - CLEANSING WIPES

10 COUNT - BUTTERFLY STRIPS

5 COUNT - TRIPLE ANTIBIOTIC PACKETS

5 COUNT - HYDROCORTISONE PACKETS

1 SET PACKETS (16 TABLETS) - IBUPROFEN

Manufactured for: Welly Health PBC
Minneapolis, MN 55402
1-833-BE-WELLY

Recycle me!

WellyTM www.GetWelly.com

Products of USA and China with globally sourced materials

Product not made with natural rubber latex

Sterile unless individual wrapper opened or damaged.

Patent Pending